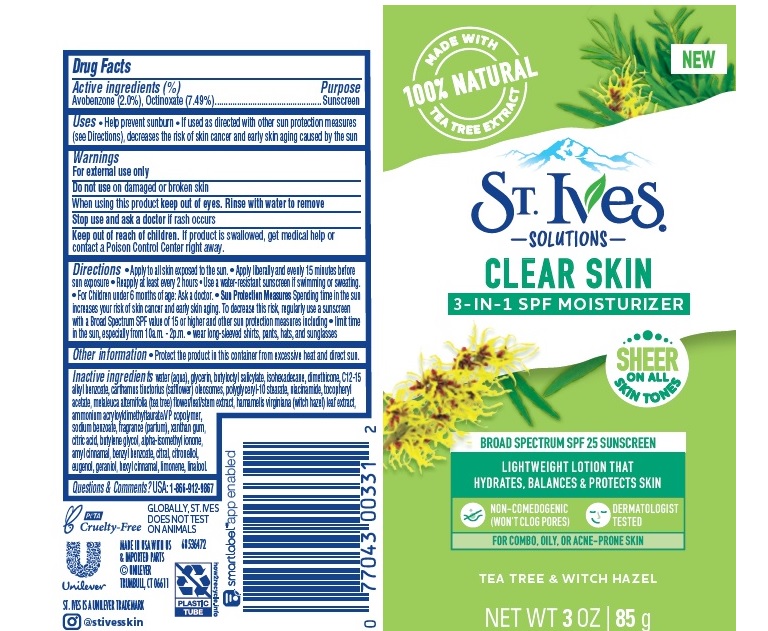 DRUG LABEL: St. Ives
NDC: 64942-1862 | Form: LOTION
Manufacturer: CONOPCO Inc. d/b/a Unilever
Category: otc | Type: HUMAN OTC DRUG LABEL
Date: 20241107

ACTIVE INGREDIENTS: OCTINOXATE 7.49 g/100 mL; AVOBENZONE 2 g/100 mL
INACTIVE INGREDIENTS: EUGENOL; ISOMETHYL-.ALPHA.-IONONE; HAMAMELIS VIRGINIANA LEAF; BENZYL BENZOATE; NIACINAMIDE; CITRAL; .ALPHA.-HEXYLCINNAMALDEHYDE; MELALEUCA ALTERNIFOLIA FLOWERING TOP; BUTYLOCTYL SALICYLATE; GLYCERIN; ISOHEXADECANE; CARTHAMUS TINCTORIUS SEED OLEOSOMES; WATER; POLYGLYCERYL-10 STEARATE; AMMONIUM ACRYLOYLDIMETHYLTAURATE/VP COPOLYMER; XANTHAN GUM; BUTYLENE GLYCOL; CITRIC ACID MONOHYDRATE; SODIUM BENZOATE; .ALPHA.-TOCOPHEROL ACETATE; DIMETHICONE; LIMONENE, (+)-; LINALOOL, (+/-)-; ALKYL (C12-15) BENZOATE; .ALPHA.-AMYLCINNAMALDEHYDE; GERANIOL; .BETA.-CITRONELLOL, (R)-

St. Ives Solutions Clear Skin 3-IN-1 Moisturizer Sunscreen SPF 25

Drug Facts

Active ingredient
Avobenzone 2%
Octinoxate 7.49%

Purpose

Sunscreen

Uses

Help prevent sunburn
If used as directed with other sun protection measures (see Directions) decreases the risk of skin cancer and early skin aging caused by the sun

Warnings

For external use only
Do not use on damaged or broken skin
When using this product keep out of eyes. Rinse with water to remove
Stop use and ask a doctor if rash occurs

KEEP OUT OF REACH OF CHILDREN

Keep out of reach of childrenf product is swallowed, get medical help or contact a Poison Control Center right away.

Directions

Apply to all skin exposed to the sun
Apply liberally and evenly 15 minutes before sun exposure
Reapply at least every 2 hours
Use a water resistant sunscreen if swimming or sweating
For Children under 6 months of age. Ask a doctor.
Sun Protection Measures Spending time in the sun increases your risk of skin cancer and early skin aging. To decrease this rish, regularly use a sunscreen with a Broad Spectum SPF value of 15 or higher and other sun protection measures including limit time in the sun, especially from 10a.m. - 2p.m. wear long-sleeved shirts, pants, hats and sunglasses

Other information

Protect the product in this container from excessive heat and direct sun

Inactive ingredients

Water (Aqua), Glycerin, Butyloctyl Salicylate, Isohexadecane, Dimethicone, C12-15 Alkyl Benzoate, Carthamus Tinctorius (Safflower) Oleosomes, Polyglyceryl-10 Stearate, Niacinamide, Tocopheryl Acetate, Melaleuca Alternifolia (Tea Tree) Flower/Leaf/Stem Extract, Hamamelis Virginiana (Witch Hazel) Leaf Extract. Ammonium Acryloyldimethyltaurate/VP Copolymer, Sodium Benzoate, Fragrance (Parfum), Xanthan Gum, Citric Acid, Butylene Glycol, Alpha-Isomethyl Ionone, Amyl Cinnamal, Benzyl Benzoate, Citral, Citronellol, Eugenol, Geraniol, Hexyl Cinnamal, Limonene, Linalool.

Questions or Comments?

USA: 1-800-912-9867